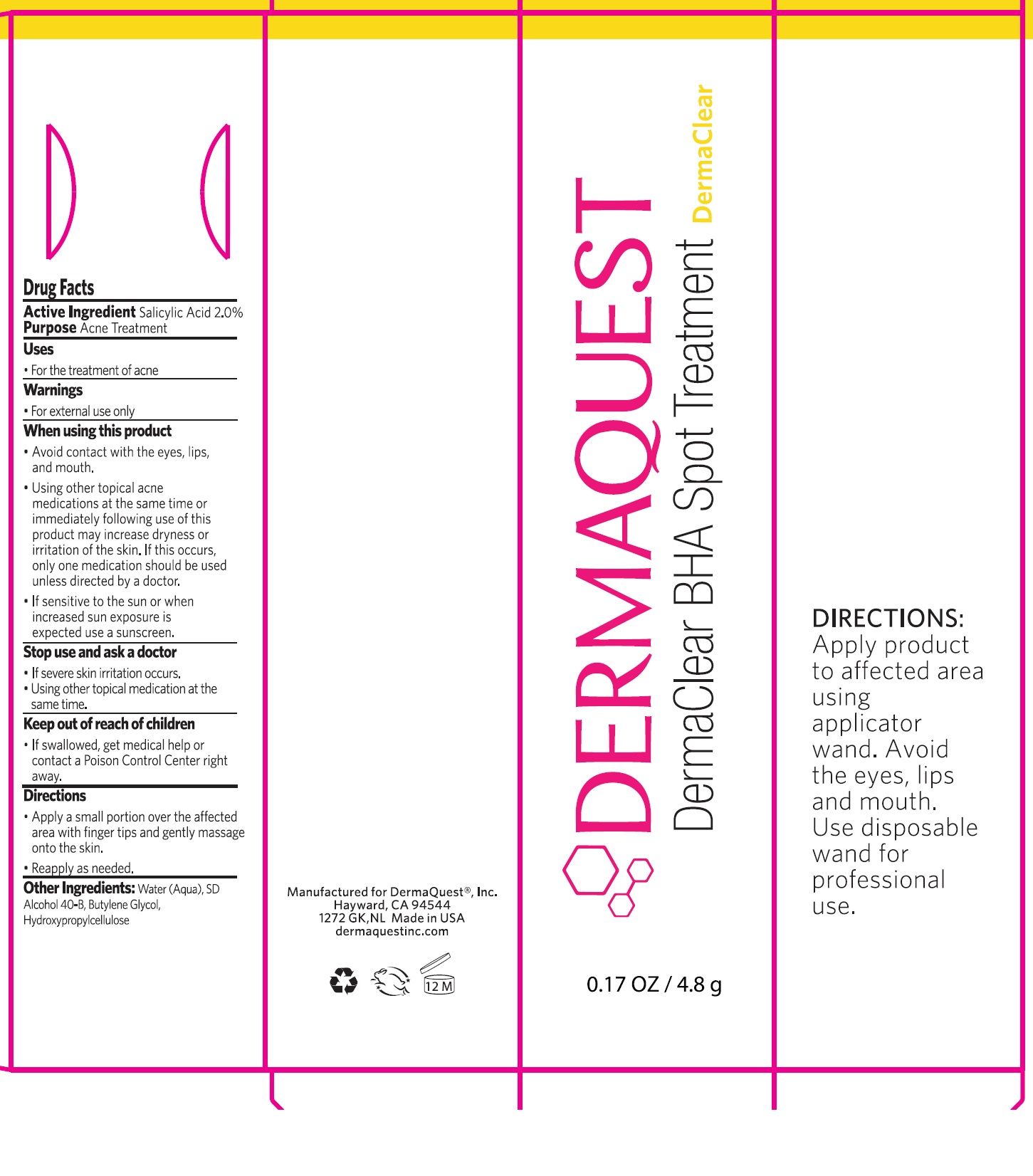 DRUG LABEL: DermaClear BHA Spot Treatment
NDC: 62742-4195 | Form: GEL
Manufacturer: Allure Labs
Category: otc | Type: HUMAN OTC DRUG LABEL
Date: 20241205

ACTIVE INGREDIENTS: SALICYLIC ACID 2 mg/1 g
INACTIVE INGREDIENTS: WATER; HYDROXYPROPYL CELLULOSE, UNSPECIFIED; ALCOHOL; BUTYLENE GLYCOL

Drug Facts

Active Ingredient: Salicylic Acid - 2%

Purpose: Acne Treatment

Uses:

- For the treatment of acne.

WARNINGS

Warnigs

- For external use only

When using this product

- Avoid contact with eyes, lips and mouth.
- Using other topical acne medication at the same time ot immefiately following use of this product may increase dryness or irritation of the skin. If this occurs only one medication should be used unless directed by a doctor.
- If sensitive to the sun or when increased sun exposure is expected use a sunscreen.

Stop use and ask a doctor:

- If severe skin irritation occurs.
- Using other topical medication at the same time

Keep out of reach of children:

- If swallowed, get medical help or contact a Poison Control Centre right away.

Directions

- Apply a small portion over the affected area with finger tips and gently massage onto the skin.
- Reapply as needed.

INACTIVE INGREDIENT

Other ingredients:

Water (aqua), SD Alcohol 40-B, Butylene Glycol, Hydroxypropylcellulose

PACKAGE LABEL

Manufactured For Dermaquest ®, Inc.

Hayward, CA 94544

1272 GK, NL Made in USA

dermaquestinc.com